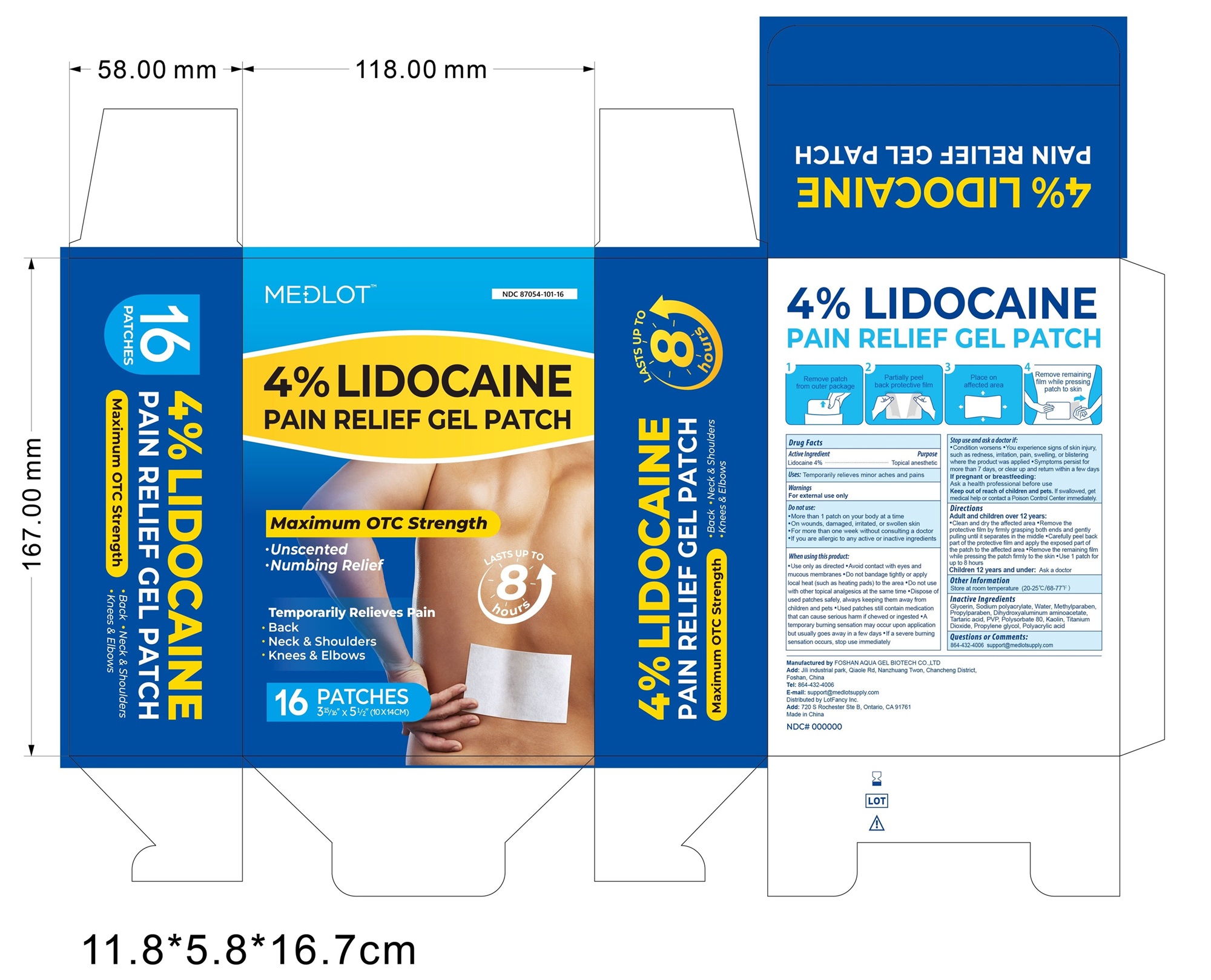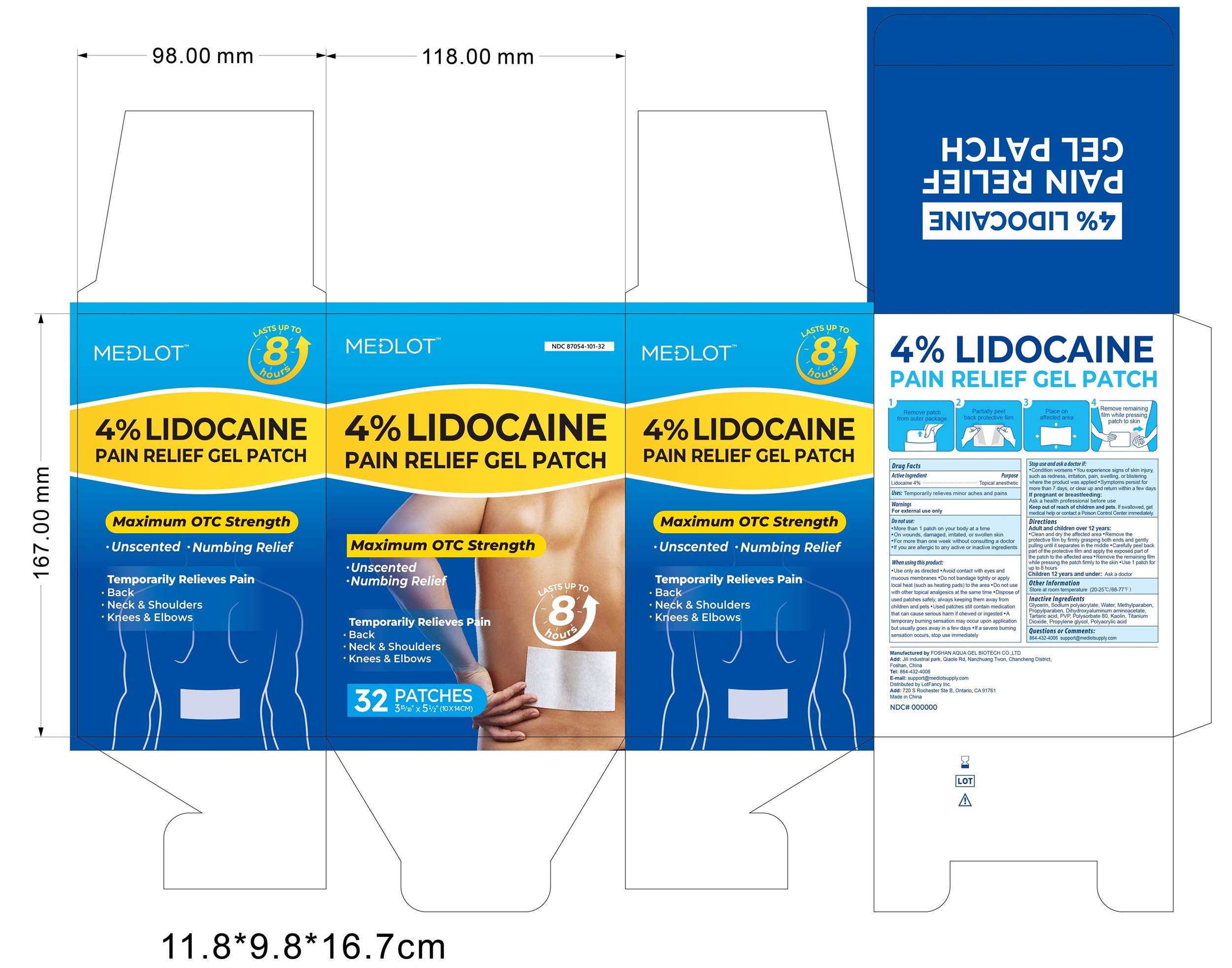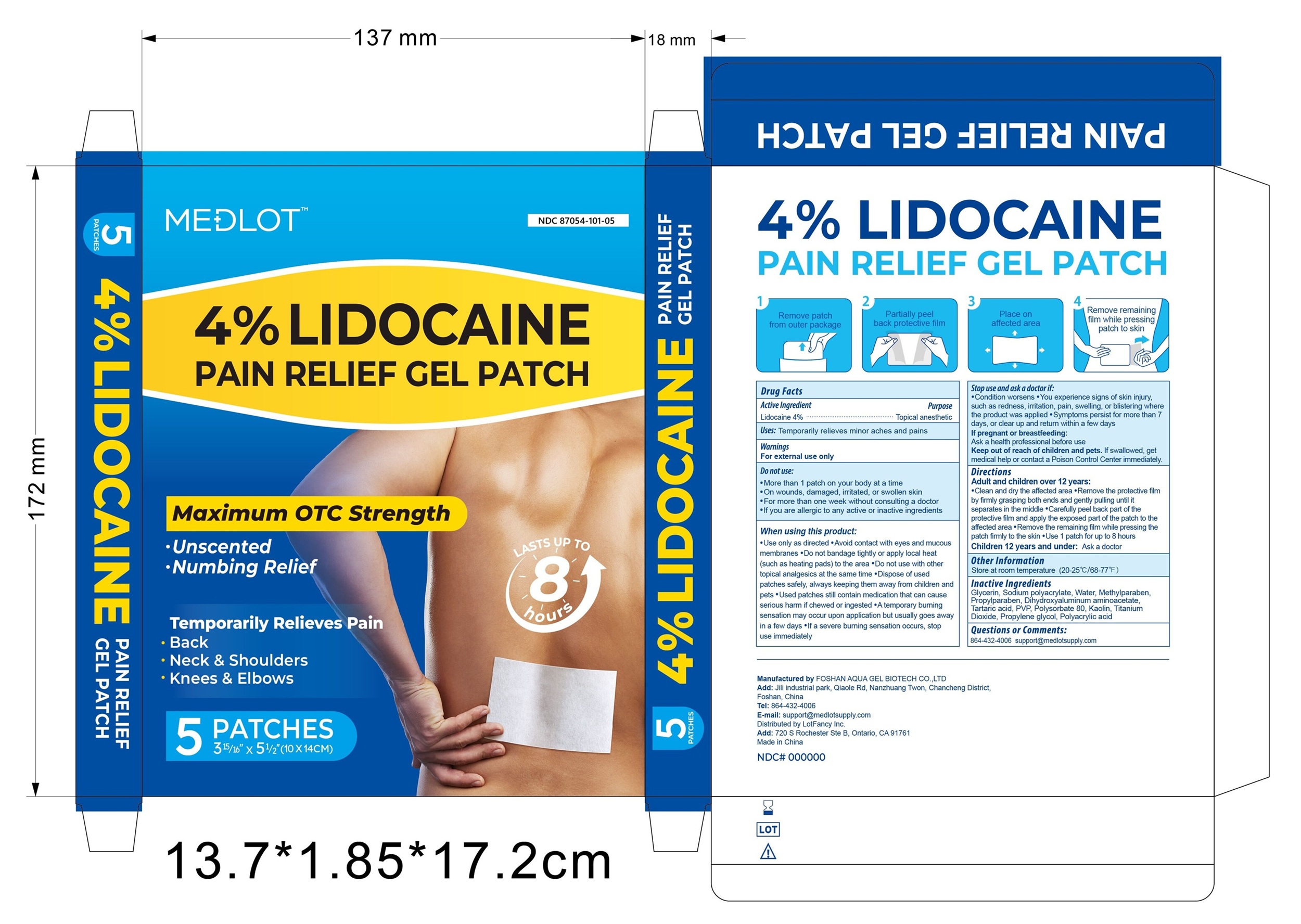 DRUG LABEL: medlot pain relief gel patch
NDC: 87054-105 | Form: PATCH, EXTENDED RELEASE
Manufacturer: Lotfancy, Inc.
Category: otc | Type: HUMAN OTC DRUG LABEL
Date: 20251223

ACTIVE INGREDIENTS: LIDOCAINE 40 mg/40 mg
INACTIVE INGREDIENTS: PVP; GLYCERIN; PROPYLPARABEN; TITANIUM DIOXIDE; WATER; TARTARIC ACID; POLYSORBATE 80; PROPYLENE GLYCOL; SODIUM POLYACRYLATE (2500000 MW); DIHYDROXYALUMINUM AMINOACETATE; POLYACRYLIC ACID (8000 MW); METHYLPARABEN; KAOLIN

Active Ingredient

Lidocaine 4%

Uses

Temporarily relieves minor aches and pains

Warnings

For external use only

Do not use:

- More than 1 patch on your body at a time
- On wounds, damaged, irritated or swollen skin
- For more than one week without consulting a doctor
- If you are allergic to any active or inactive ingredients

When using this product:

- Use only as directed
- Avoid contact with eyes and mucous membranes
- Do not bandage tightly or apply local heat (such as heating pads) to the area
- Do not use with other topical analgesics at the same time
- Dispose of used patches safely, always keeping them away from children and pets
- Used patches still contain medication that can cause serious harm if chewed or ingested
- A temporary burning sensation may occur upon application but usually goes away in a few days
- If a severe burning sensation occurs, stop use immediately

Stop use and ask a doctor if:

- Condition worsens
- You experience signs of skin injury, such as redness, irritation, pain, swelling, or blistering where the product was applied
- Symptoms persist for more than 7 days, or clear up and return within a few days

If pregnant or breastfeeding

Ask a healthcare professional before use

Keep out of reach of children and pets.

If swallowed, get medical help or contact a Poison Control Center immediately

Directions

Adults and children over 12 years:

- Clean and dry the affected area
- Remove the protective film by firmly grasping both ends and gently puling until it separate in the middle
- Carefully peel back part of the protective film and apply the exposed part of the patch to the affected area
- Remove the remaining film while pressing the patch firmly to the skin
- Use 1 patch for up to 8 hours

Children 12 years and under: Ask a doctor

Other Information

Store at room temperature (20-25 C / 68-77 F)

Inactive Ingredients

Glycerin, Sodium polyacrylate, Water, Methylparaben, Propylparaben, Dihydroxyaluminum aminoacetate, Tartaric acid, PVP, Polysorbate 80, Kaolin, Titanium Dioxide, Propylene glycol, Polyacrylic acid

Questions or Comments

864-432-4006 support@medlotsupply.com

Administration

Remove patch from outer package.

Partially peel back protective film.

Place on affected area.

Remove remaining film while pressing patch to skin.

Uses

Temporarily Relieves minor aches and pains.

- Back
- Neck & Shoulders
- Knees & Elbows

RECENT MAJOR CHANGES

image of packaging uploaded